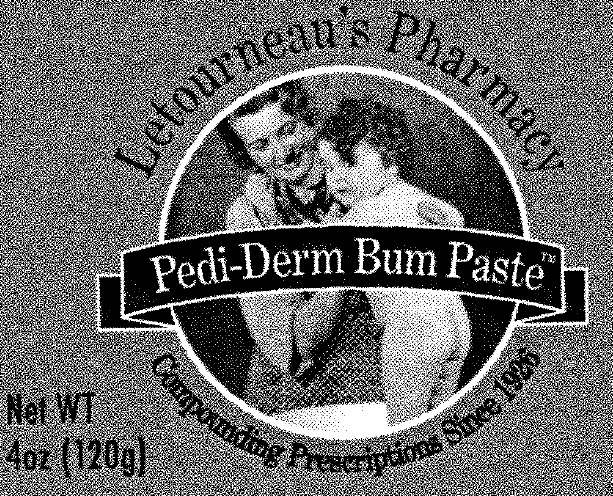 DRUG LABEL: Pedi-Derm Bum
NDC: 69715-100 | Form: PASTE
Manufacturer: Elixir Solutions, Inc.
Category: otc | Type: HUMAN OTC DRUG LABEL
Date: 20231220

ACTIVE INGREDIENTS: ZINC OXIDE 25 g/100 g
INACTIVE INGREDIENTS: BISMUTH SUBGALLATE; LEVANT COTTONSEED OIL; LANOLIN; STARCH, CORN

Letourneau’s Pharmacy
Pedi-Derm Bum Paste

Active Ingredient

Zinc Oxide (CI 77947) 25%

Purpose

Skin Protectant

Uses:

Treats diaper rash and skin irritations

Warnings

For external use only. Do not use in the eyes or if you allergic to any of the ingredients. Stop use and ask a doctor if you need to use longer than 1 week or condition worsens.

Keep out of reach of children.

If swallowed get medical help or contact Poison Control Center right away.

Directions:

Apply a thick coat after diaper change, especially at bedtime. If baby cries during application it is because of their sensitive skin, this product does not sting. Use soft cloth or paper towel to clean bottom.

Other Information:

Do not store in conditions of excess humidity or heat beyond 42°C (107°F).
Do not use if seal under cap is missing or broken.

Inactive Ingredients:

Bismuth Subgallate, Gossypium Herbaceum (Cotton) Seed Oil, Lanolin, Zea Mays (Corn) Starch.

Principal Display Panel - Carton Label

Letourneau’s Pharmacy
Pedi-Derm Bum Paste™
Compounding Prescriptions Since 1926

Net WT
4oz (120g)